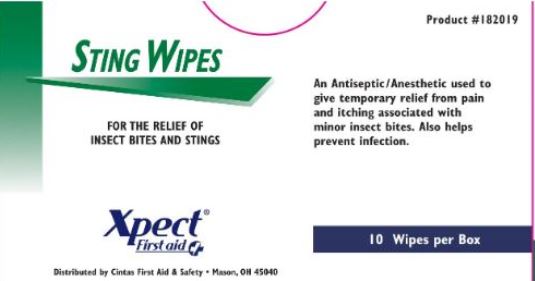 DRUG LABEL: Xpect Sting Wipes
NDC: 42961-182 | Form: SWAB
Manufacturer: Cintas Corporation
Category: otc | Type: HUMAN OTC DRUG LABEL
Date: 20250926

ACTIVE INGREDIENTS: BENZOCAINE 6 g/100 1
INACTIVE INGREDIENTS: ALCOHOL 60 g/100 1

Xpect Sting Wipes

Active ingredient (in each towelette)

Benzocaine 6%

Purpose

External analgesic

Uses

for the temporary relief of pain and itching associated with insect bites

Warnings

- For external use only
- Flammable keep away from fire or flame

Do not use

- in the eyes
- on broken skin
- for deep puncture wounds

Stop use and ask a doctor if

- condition gets worse
- condition clears up and recurs within a few days
- condition persists for more than 7 days
- unusual redness, swelling, or irritation occurs

Keep out of reach of children. If swallowed, get medical help or contact a Poison Control Center right away.

Directions

Adults and children over 2 years: apply to affected area not more than 3-4 times daily
Children under 2 years: consult a doctor

Other information

• do not use if packet is torn, cut, or opened
• Store at room temperature.

Inactive ingredients

SD alcohol 60%

Questions?

1-877-973-2811

Box Principal Display Panel

STING WIPES

FOR THE RELIEF OF INSECT BITES AND STINGS

Xpect® First aid

Distributed by Cintas First Aid & Safety • Mason, OH 45040

Product #182019

An Antiseptic/Anesthetic used to give temporary relief from pain and itching associated with minor insect bites. Also helps prevent infection.

10 Wipes per Box